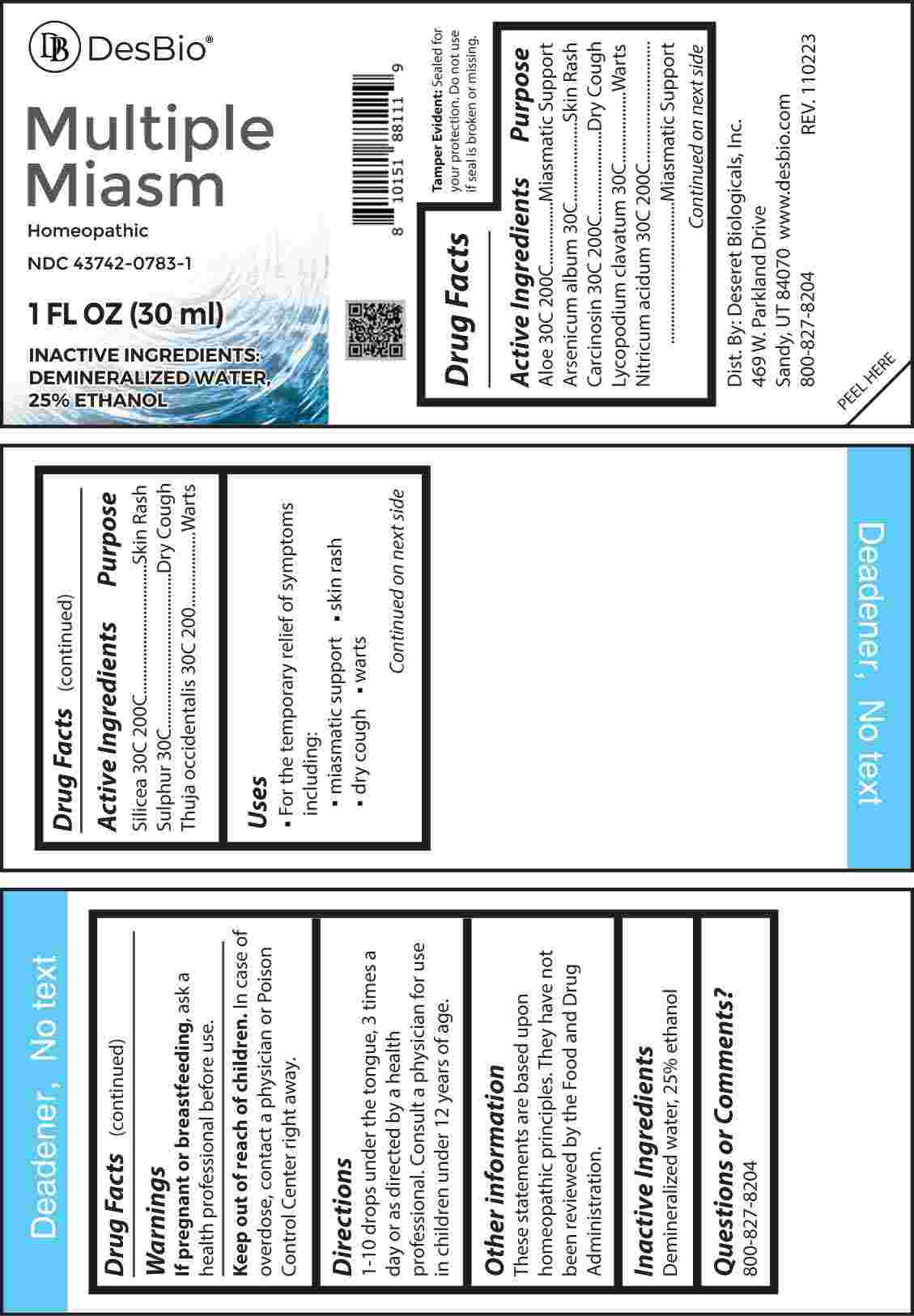 DRUG LABEL: Multiple Miasm
NDC: 43742-0783 | Form: LIQUID
Manufacturer: Deseret Biologicals, Inc.
Category: homeopathic | Type: HUMAN OTC DRUG LABEL
Date: 20240509

ACTIVE INGREDIENTS: ARSENIC TRIOXIDE 30 [hp_C]/1 mL; LYCOPODIUM CLAVATUM SPORE 30 [hp_C]/1 mL; SULFUR 30 [hp_C]/1 mL; ALOE 30 [hp_C]/1 mL; HUMAN BREAST TUMOR CELL 30 [hp_C]/1 mL; NITRIC ACID 30 [hp_C]/1 mL; SILICON DIOXIDE 30 [hp_C]/1 mL; THUJA OCCIDENTALIS LEAF 30 [hp_C]/1 mL
INACTIVE INGREDIENTS: WATER; ALCOHOL

DRUG FACTS:

ACTIVE INGREDIENTS:

Aloe 30C, 200C, Arsenicum Album 30C, Carcinosin 30C, 200C, Lycopodium Clavatum 30C, Nitricum Acidum 30C, 200C, Silicea 30C, 200C, Sulphur 30C, Thuja Occidentalis 30C, 200C.

PURPOSE:

Aloe – Miasmatic Support, Arsenicum Album – Skin Rash, Carcinosin – Dry Cough, Lycopodium Clavatum - Warts, Nitricum Acidum – Miasmatic Support, Silicea – Skin Rash, Sulphur – Dry Cough, Thuja Occidentalis - Warts

USES:

• For the temporary relief of symptoms including:

• miasmatic support • skin rashes

• dry coughs • warts

These statements are based upon homeopathic principles. They have not been reviewed by the Food and Drug Administration.

WARNINGS:

If pregnant or breast-feeding, ask a health professional before use.

Keep out of reach of children. In case of overdose contact a physician or Poison Control Center right away.

Tamper Evident: Sealed for your protection. Do not use if seal is broken or missing.

KEEP OUT OF REACH OF CHILDREN:

In case of overdose, contact a physician or Poison Control Center right away.

DIRECTIONS:

1-10 drops under the tongue, 3 times a day or as directed by a health professional. Consult a physician for use in children under 12 years of age.

INACTIVE INGREDIENTS:

Demineralized water, 25% ethanol

QUESTIONS:

Dist. By: Deseret Biologicals, Inc.

469 W. Parkland Drive

Sandy, UT 84070

www.desbio.com

800-827-8204

PACKAGE LABEL DISPLAY:

Des Bio

Multiple

Miasm

Homeopathic

NDC 43742-0783-1

1 FL OZ (30 ml)